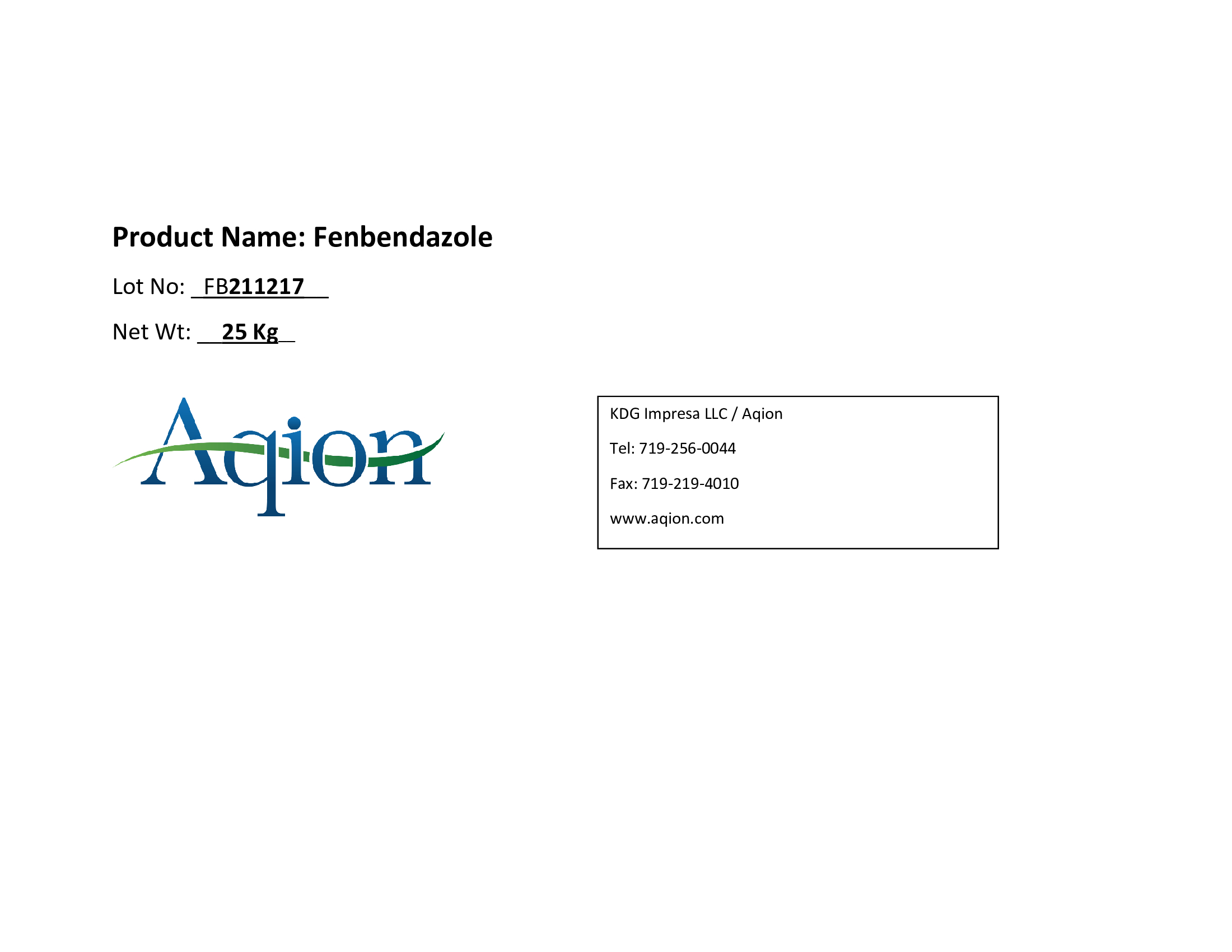 DRUG LABEL: Fenbendazole
NDC: 43457-650 | Form: POWDER
Manufacturer: KDG Impresa LLC, Aqion
Category: other | Type: BULK INGREDIENT - ANIMAL DRUG
Date: 20231020

ACTIVE INGREDIENTS: Fenbendazole 1 kg/1 kg

Fenbendazole